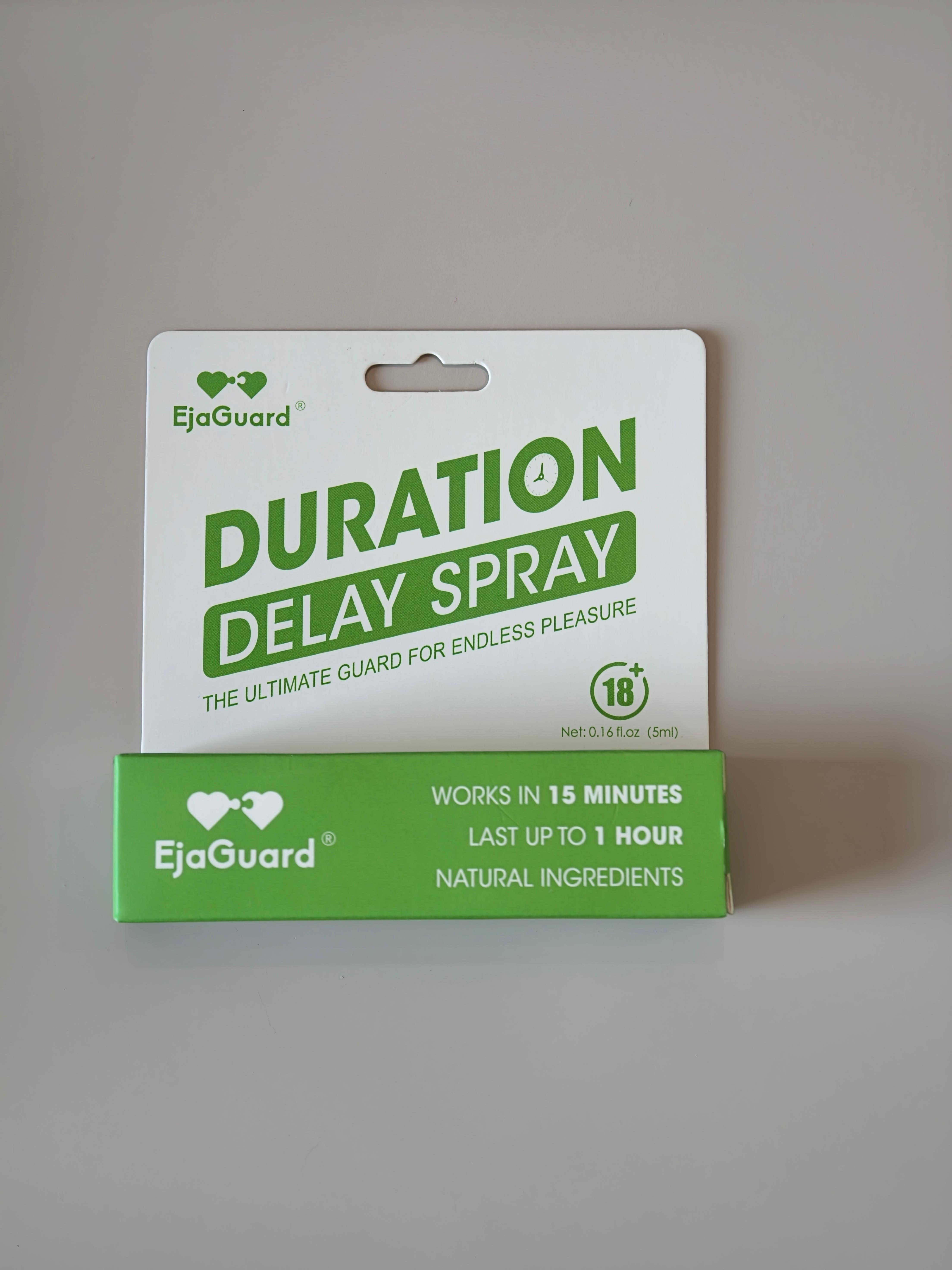 DRUG LABEL: EjaGuard
NDC: 87297-2601 | Form: SPRAY
Manufacturer: MOLANSPACE INC
Category: otc | Type: HUMAN OTC DRUG LABEL
Date: 20260101

ACTIVE INGREDIENTS: LIDOCAINE 9.6 g/100 g
INACTIVE INGREDIENTS: AQUA 50 g/100 g; STEARIC ACID 3 g/100 g; ISOPROPYL MYRISTATE 12 g/100 g; ETHOXYDIGLYCOL 25 g/100 g; FRAGRANCE CLEAN ORC0600327 0.4 g/100 g

Active ingredient

Lidocaine 9.6%

Purpose

Desensitizer

Uses

- Helps in the prevention of premature ejaculation.
- Helps in temporarily prolonging the time until ejaculation.

Warnings

- For external use only.
- Premature ejaculation may be due to a condition requiring medical supervision. If this product, used as directed, does not provide relief, discontinue use and consult a doctor.

When using this product

Avoid contact with the eyes.

Stop use and ask a doctor if

You or your partner develop a rash or irritation, such as burning or itching. If symptoms persist, consult a doctor.

If pregnant or breast-feeding

Ask a health professional before use.

Keep out of reach of children

If swallowed, get medical help or contact a Poison Control Center right away.

Directions

- Clean and dry the penis.
- Apply 3 to 10 sprays to the penis head and shaft.
- Wait 15 to 30 minutes for full absorption before intercourse.
- Wash product off after intercourse.

Inactive ingredients

AQUA, ETHOXYDIGLYCOL, ISOPROPYL MYRISTATE, STEARIC ACID, FRAGRANCE.

Other information

- Store at room temperature 15°-30°C (59°-86°F).
- Protect from excessive heat and direct sun.

Questions or comments?

213-396-1046 / MalachiPerez291@gmail.com

Box Front Panel

EjaGuard
DURATION DELAY SPRAY
Net: 0.16fl.oz (5ml)
WORKS IN 15 MINUTES
LAST UP TO 1 HOUR
NATURAL INGREDIENTS